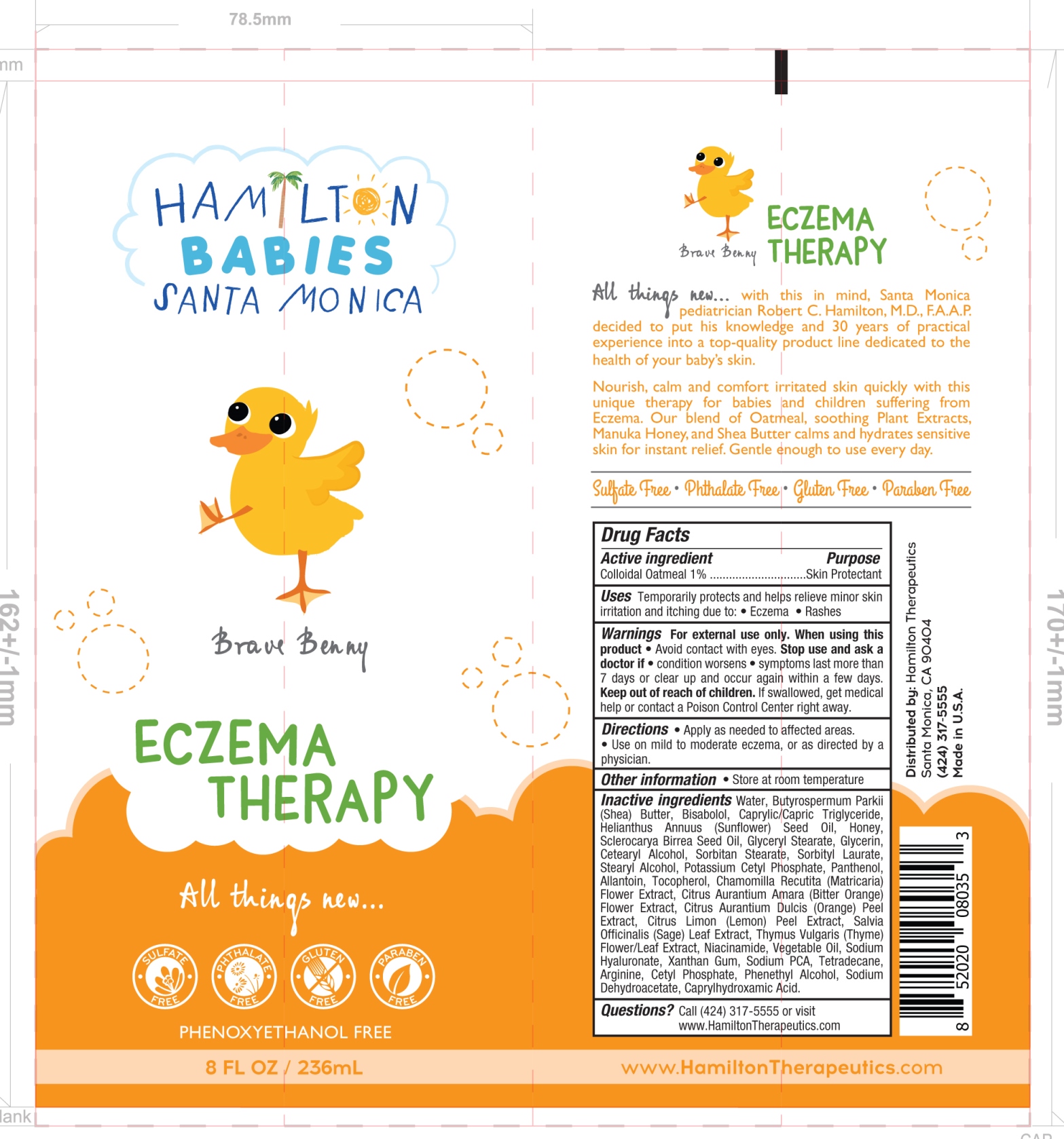 DRUG LABEL: Eczema Therapy
NDC: 72381-103 | Form: CREAM
Manufacturer: Hamilton Therapeutics, Inc.
Category: otc | Type: HUMAN OTC DRUG LABEL
Date: 20230210

ACTIVE INGREDIENTS: OATMEAL 1 g/100 mL
INACTIVE INGREDIENTS: SORBITYL LAURATE; CHAMOMILE; ARGININE; PHENYLETHYL ALCOHOL; ALCOHOL; LEMON PEEL; SAGE; NIACINAMIDE; CETYL PHOSPHATE; PANTHENOL; ALLANTOIN; TOCOPHEROL; SHEA BUTTER; CITRUS AURANTIUM FLOWER; CORN OIL; HYALURONATE SODIUM; SODIUM PYRROLIDONE CARBOXYLATE; TETRADECENE; SODIUM DEHYDROACETATE; CAPRYLHYDROXAMIC ACID; SUNFLOWER OIL; HONEY; XANTHAN GUM; ORANGE PEEL; THYME; LEVOMENOL; MEDIUM-CHAIN TRIGLYCERIDES; SCLEROCARYA BIRREA SEED OIL; GLYCERYL MONOSTEARATE; GLYCERIN; CETOSTEARYL ALCOHOL; SORBITAN MONOSTEARATE; STEARYL ALCOHOL; POTASSIUM CETYL PHOSPHATE

Eczema Therapy

Active ingredient Purpose
Colloidal Oatmeal 1% ..............................Skin Protectant

Uses

Temporarily protects and helps relieve minor skin
irritation and itching due to: • Eczema • Rashes

Keep out of reach of children. If swallowed, get medical
help or contact a Poison Control Center right away.

Stop use and ask a doctor if

• condition worsens

• symptoms last more than 7 days or clear up and occur again within a few days

WARNINGS

Warnings For external use only. When using this product • Avoid contact with eyes.

DOSAGE AND ADMINISTRATION

Directions • Apply as needed to affected areas.
• Use on mild to moderate eczema, or as directed by a physician.

INACTIVE INGREDIENT

Inactive ingredients Water, Butyrospermum Parkii (Shea) Butter, Bisabolol, Caprylic/Capric Triglyceride, Helianthus Annuus (Sunflower) Seed Oil, Honey, Sclerocarya Birrea Seed Oil, Glyceryl Stearate, Glycerin, Cetearyl Alcohol, Sorbitan Stearate, Sorbityl Laurate, Stearyl Alcohol, Potassium Cetyl Phosphate, Panthenol, Allantoin, Tocopherol, Chamomilla Recutita (Matricaria) Flower Extract, Citrus Aurantium Amara (Bitter Orange) Flower Extract, Citrus Aurantium Dulcis (Orange) Peel Extract, Citrus Limon (Lemon) Peel Extract, Salvia Officinalis (Sage) Leaf Extract, Thymus Vulgaris (Thyme) Flower/Leaf Extract, Niacinamide, Vegetable Oil, Sodium Hyaluronate, Xanthan Gum, Sodium PCA, Tetradecane, Arginine, Cetyl Phosphate, Phenethyl Alcohol, Sodium Dehydroacetate, Caprylhydroxamic Acid.

PACKAGE LABEL

Eczema Therapy

8 FL OZ/ 236mL